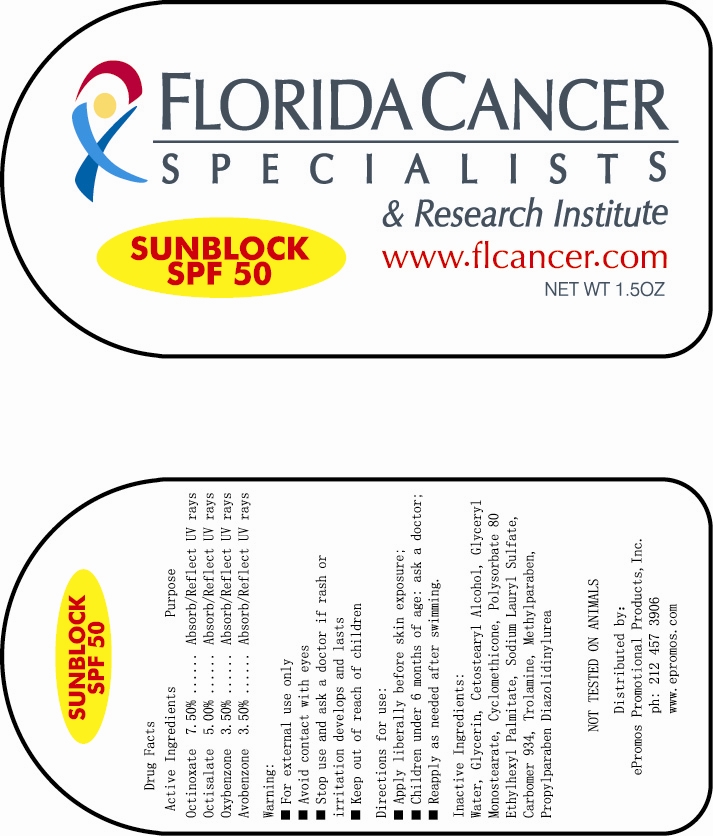 DRUG LABEL: Correway Sunscreen (Non-waterproof)
NDC: 50600-004 | Form: CREAM
Manufacturer: Ningbo Correway Cosmetics Co., Ltd.
Category: otc | Type: HUMAN OTC DRUG LABEL
Date: 20100720

ACTIVE INGREDIENTS: Octinoxate 75 mg/1 g; Octisalate 50 mg/1 g; Oxybenzone 35 mg/1 g; Avobenzone 35 mg/1 g
INACTIVE INGREDIENTS: Water; Glycerin; Cetostearyl Alcohol; Glyceryl Monostearate; Cyclomethicone; Polysorbate 80; Ethylhexyl Palmitate; Sodium Lauryl Sulfate; Carbomer 934; Trolamine; Methylparaben; Propylparaben; Diazolidinyl Urea

Drug Facts

ACTIVE INGREDIENT

Octinoxate, Octisalate, Oxybenzone, Avobenzone

Stop use and ask a doctor if rash or irritation develops and lasts;
Children under 6 months of age: ask a doctor;

DO NOT USE

Avoid contact with eyes;
Stop use and ask a doctor if rash or irritation develops and lasts;

Keep out of reach of children;

PURPOSE

Helps prevent sunburn;
Higher SPF gives more sunburn protection;
Rinse with water to remove;

WHEN USING

Apply liberally before skin exposure;
Reapply as needed after swimming;

Stop use and ask a doctor if rash or irritation develops and lasts;

PACKAGE LABEL

Active Ingredients Purpose
Octinoxate 7.50% ………………………………… Absorb/Reflect UV rays
Octisalate 5.00% ………………………………… Absorb/Reflect UV rays
Oxybenzone 3.50% ………………………………… Absorb/Reflect UV rays
Avobenzone 3.50% ………………………………… Absorb/Reflect UV rays
Uses:
■ Helps prevent sunburn;
■ Higher SPF gives more sunburn protection;
■ Rinse with water to remove
Warning:
■ For external use only
■ Avoid contact with eyes
■ Stop use and ask a doctor if rash or irritation develops and lasts.
■ Keep out of reach of children
Directions for use:
■ Apply liberally before skin exposure;
■ Children under 6 months of age: ask a doctor;
■ Reapply as needed after swimming.
Inactive Ingredients:
Water, Glycerin, Cetostearyl Alcohol, Glyceryl Monostearate, Cyclomethicone, Polysorbate 80
Ethylhexyl Palmitate, Sodium Lauryl Sulfate, Carbomer 934, Trolamine, Methylparaben, Propylparaben
Diazolidinylurea
Distributed By:
ePromos Promotional Products, Inc.
ph: 212 457 3906
Made in China